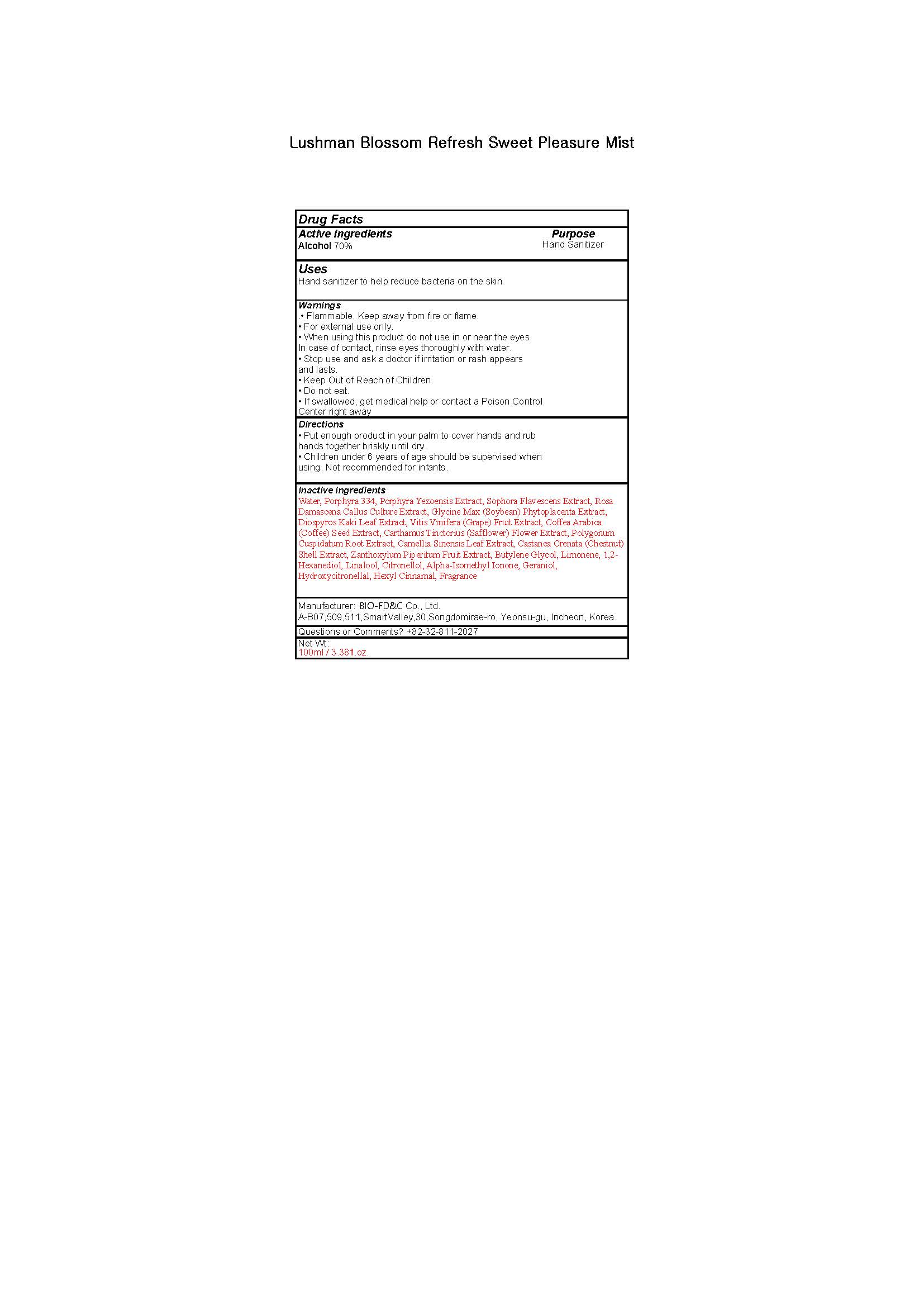 DRUG LABEL: Lushman Blossom Refresh Sweet Pleasure Mist
NDC: 76882-0005 | Form: LIQUID
Manufacturer: BIO-FD&C. Co., Ltd.
Category: otc | Type: HUMAN OTC DRUG LABEL
Date: 20200506

ACTIVE INGREDIENTS: ALCOHOL 70 mL/100 mL
INACTIVE INGREDIENTS: BUTYLENE GLYCOL; GERANIOL; WATER; 1,2-HEXANEDIOL

PACKAGE LABEL

PURPOSE

Antiseptic

ACTIVE INGREDIENT

Alcohol

INACTIVE INGREDIENT

Water, Porphyra 334, Porphyra Yezoensis Extract, Sophora Flavescens Extract, Rosa Damascena Callus Culture Extract, Glycine Max (Soybean) Phytoplacenta Extract, Diospyros Kaki Leaf Extract, Vitis Vinifera (Grape) Fruit Extract, Coffea Arabica (Coffee) Seed Extract, Carthamus Tinctorius (Safflower) Flower Extract, Polygonum Cuspidatum Root Extract, Camellia Sinensis Leaf Extract, Castanea Crenata (Chestnut) Shell Extract, Zanthoxylum Piperitum Fruit Extract, Butylene Glycol, Limonene, 1,2
Hexanediol, Linalool, Citronellol, Alpha Isomethyl Ionone, Geraniol, Hydroxycitronellal, Hexyl Cinnamal, Fragrance

DOSAGE AND ADMINISTRATION

For the external use only

WARNINGS

.• Flammable. Keep away from fire or flame.
• For external use only.
• When using this product do not use in or near the eyes.
In case of contact, rinse eyes thoroughly with water.
• Stop use and ask a doctor if irritation or rash appears
and lasts.
• Keep Out of Reach of Children.
• Do not eat.
• If swallowed, get medical help or contact a Poison Control
Center right away

Directions
• Put enough product in your palm to cover hands and rub
hands together briskly until dry.
• Children under 6 years of age should be supervised when
using. Not recommended for infants.

Keep out of reach of children